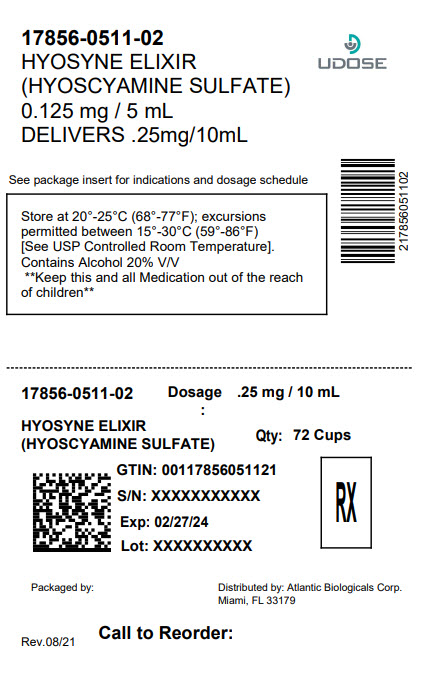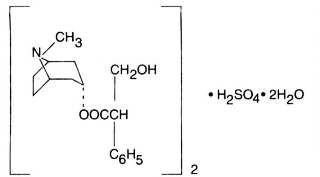 DRUG LABEL: Hyosyne
NDC: 17856-0511 | Form: ELIXIR
Manufacturer: ATLANTIC BIOLOGICALS CORP.
Category: prescription | Type: HUMAN PRESCRIPTION DRUG LABEL
Date: 20250512

ACTIVE INGREDIENTS: HYOSCYAMINE SULFATE 0.125 mg/5 mL
INACTIVE INGREDIENTS: ALCOHOL; ANHYDROUS CITRIC ACID; FD&C RED NO. 40; FD&C YELLOW NO. 6; GLYCERIN; SODIUM BENZOATE; SODIUM CITRATE, UNSPECIFIED FORM; SORBITOL; SUCROSE; WATER

HYOSYNE ORAL DROPS
(Hyoscyamine Sulfate Oral Solution)
HYOSYNE ELIXIR
(Hyoscyamine Sulfate Elixir)

DESCRIPTION

HYOSYNE ORAL DROPS(Hyoscyamine Sulfate Oral Solution) contain 0.125 mg hyoscyamine sulfate per
mL with 5% v/v alcohol for oral administration.

HYOSYNE ELIXIR(Hyoscyamine Sulfate Elixir) contains 0.125 mg hyoscyamine sulfate per 5 mL with
20% v/v alcohol for oral administration.

Hyoscyamine sulfate is one of the principal anticholinergic/antispasmodic components of belladonna alkaloids. The empirical formula is (C17H23NO3)2• H2SO4• 2H2O and the molecular weight is 712.85. Chemically, it is benzeneacetic acid, (α-(hydroxymethyl)-,8-methyl-8-azabicyclo [3.2.1.] oct-3-yl ester, [3(S)-endo]-,sulfate (2:1), dihydrate with the following structure:

HYOSYNE ORAL DROPSalso contain as inactive ingredients: Alcohol, citric acid, FD&C red #40, FD&C yellow #6, flavor, glycerin, sodium benzoate, sodium citrate, sorbitol solution, sucrose, and water.

HYOSYNE ELIXIRalso contain as inactive ingredients: Alcohol, citric acid, FD&C red #40, FD&C yellow #6, flavor, glycerin, purified water, sodium benzoate, sodium citrate, sorbitol solution, and sucrose.

CLINICAL PHARMACOLOGY

Hyoscyamine Sulfate inhibits specifically the actions of acetylcholine on structures innervated by postganglionic cholinergic nerves and on smooth muscles that respond to acetylcholine but lack cholinergic innervation. These peripheral cholinergic receptors are present in the autonomic effector cells of the smooth muscle, cardiac muscle, the sinoatrial node, the atrioventricular node, and the exocrine glands. At therapeutic doses, it is completely devoid of any action on autonomic ganglia. Hyoscyamine sulfate
inhibits gastrointestinal propulsive motility and decreases gastric acid secretion. Hyoscyamine sulfate also controls excessive pharyngeal, tracheal and bronchial secretions.

Hyoscyamine sulfate is absorbed totally and completely by oral administration. Once absorbed, hyoscyamine sulfate disappears rapidly from the blood and is distributed throughout the entire body. The half-life of hyoscyamine sulfate is 2 to 3 1/2 hours. Hyoscyamine sulfate is partly hydrolyzed to tropic acid and tropine but the majority of the drug is excreted in the urine unchanged within the first 12 hours. Only traces of this drug are found in breast milk. Hyoscyamine sulfate passes the blood brain barrier and the placental barrier.

INDICATIONS AND USAGE

Hyoscyamine sulfate is effective as adjunctive therapy in the treatment of peptic ulcer. It can also be used to control gastric secretion, visceral spasm and hypermotility in spastic colitis, spastic bladder, cystitis, pylorospasm, and associated abdominal cramps. May be used in functional intestinal disorders to reduce symptoms such as those seen in mild dysenteries, diverticulitis, and acute enterocolitis. For use as adjunctive therapy in the treatment of irritable bowel syndrome (irritable colon, spastic colon,
mucous colitis) and functional gastrointestinal disorders. Also used as adjunctive therapy in the treatment of neurogenic bladder and neurogenic bowel disturbances (including the splenic flexure syndrome and neurogenic colon). Also used in the treatment of infant colic (elixir and drops). Hyoscyamine sulfate is indicated along with morphine or other narcotics in symptomatic relief of biliary and renal colic; as a “drying agent” in the relief of symptoms of acute rhinitis; in the therapy of parkinsonism to reduce rigidity and tremors and to control associated sialorrhea and hyperhidrosis. May be used in the therapy of poisoning by anticholinesterase agents.

CONTRAINDICATIONS

Glaucoma; obstructive uropathy (for example, bladder neck obstruction due to prostatic hypertrophy); obstructive disease of the gastrointestinal tract (as in achalasia, pyloroduodenal stenosis); paralytic ileus, intestinal atony of elderly or debilitated patients; unstable cardiovascular status in acute hemorrhage; severe ulcerative colitis; toxic megacolon complicating ulcerative colitis; myasthenia gravis.

WARNINGS

In the presence of high environmental temperature, heat prostration can occur with drug use (fever and heat stroke due to decreased sweating). Diarrhea may be an early symptom of incomplete intestinal obstruction, especially in patients with ileostomy or colostomy. In this instance, treatment with this drug would be inappropriate and possibly harmful. Like other anticholinergic agents, Hyoscyamine sulfate may produce drowsiness, dizziness or blurred vision. In this event, the patient should be warned not to engage in activities requiring mental alertness such as operating a motor vehicle or other machinery or to perform hazardous work while taking this drug.

Psychosis has been reported in sensitive individuals given anticholinergic drugs. CNS signs and symptoms include confusion, disorientation, short term memory loss, hallucinations, dysarthria, ataxia, coma, euphoria, decreased anxiety, fatigue, insomnia, agitation and mannerisms, and inappropriate affect. These CNS signs and symptoms usually resolve within 12 to 48 hours after discontinuation of the drug.

PRECAUTIONS

General:
Use with caution in patients with: autonomic neuropathy, hyperthyroidism, coronary heart disease, congestive heart failure, cardiac arrythmias, hypertension, and renal disease. Investigate any tachycardia before giving any anticholinergic drug since they may increase the heart rate. Use with caution in patients with hiatal hernia associated with reflux esophagitis.

Information for Patients:
Like other anticholinergic agents, hyoscyamine sulfate may produce drowsiness, dizziness or blurred vision. In this event, the patient should be warned not to engage in activities requiring mental alertness such as operating a motor vehicle or other machinery or to perform hazardous work while taking this drug. Use of hyoscyamine sulfate may decrease sweating resulting in heat prostration, fever or heat stroke; febrile patients or those who may be exposed to elevated environmental temperatures should use caution.

Drug Interactions:
Additive adverse effects resulting from cholinergic blockade may occur when hyoscyamine sulfate is administered concomitantly with other antimuscarinics, amantadine, haloperidol, phenothiazines, monoamine oxidase (MAO) inhibitors, tricyclic antidepressants or some antihistamines.

Antacids may interfere with the absorption of hyoscyamine sulfate. Administer hyoscyamine sulfate before meals; antacids after meals.

Carcinogenesis, Mutagenesis, Impairment of Fertility:
No long-term studies in animals have been performed to determine the carcinogenic, mutagenic or impairment of fertility potential of hyoscyamine sulfate; however, years of marketing experience with hyoscyamine sulfate shows no demonstrable evidence of a problem.

Pregnancy - Pregnancy Category C:
Animal reproduction studies have not been conducted with hyoscyamine sulfate. It is also not known whether hyoscyamine sulfate can cause fetal harm when administered to a pregnant woman or can affect reproduction capacity. Hyoscyamine sulfate should be given to a pregnant woman only if clearly needed.

Nursing Mothers:
Hyoscyamine sulfate is excreted in human milk. Caution should be exercised when hyoscyamine sulfate is administered to a nursing woman.

Geriatric Use:
Reported clinical experience has not identified differences in safety between patients aged 65 and over and younger patients. In general, dose selection for an elderly patient should be cautious, usually starting at the low end of the dosing range, reflecting the greater frequency of decreased hepatic, renal, or cardiac function, and of concomitant disease or other drug therapy.

This drug is known to be substantially excreted by the kidney, and the risk of toxic reactions to this drug may be greater in patients with impaired renal function. Because elderly patients are more likely to have decreased renal function, care should be taken in dose selection, and it may be useful to monitor renal function.

ADVERSE REACTIONS

All of the following adverse reactions have been reported with hyoscyamine sulfate. Adverse reactions may include dryness of the mouth; urinary hesitancy and retention; blurred vision; tachycardia; palpitations; mydriasis; increased ocular tension; loss of taste; headache; nervousness; drowsiness; weakness; fatigue; dizziness; insomnia; nausea; vomiting; impotence; constipation; bloated feeling; abdominal pain; diarrhea; allergic reactions or drug idiosyncrasies; urticaria and other dermal manifestations; ataxia; speech disturbance; some degree of mental confusion and/or excitement (especially in elderly persons); short-term memory loss; hallucinations; and decreased sweating.

OVERDOSAGE

The signs and symptoms of overdose are headache, nausea, vomiting, blurred vision, dilated pupils, hot dry skin, dizziness, dryness of the mouth, difficulty in swallowing, and CNS stimulation.

Measures to be taken are immediate lavage of the stomach and injection of physostigmine 0.5 to 2 mg intravenously and repeated as necessary up to a total of 5 mg. Fever may be treated symptomatically (tepid water sponge baths, hypothermic blanket). Excitement to a degree which demands attention may be managed with sodium thiopental 2% solution given slowly intravenously or chloral hydrate (100-200 mL of a 2% solution) by rectal infusion. In the event of progression of the curare-like effect to paralysis of the respiratory muscles, artificial respiration should be instituted and maintained until effective respiratory action returns.

DOSAGE AND ADMINISTRATION

HYOSYNE ORAL DROPS
(Hyoscyamine Sulfate Oral Solution)

Dosage may be adjusted according to the conditions and severity of symptoms. Measuredosage very carefully.
Adults and pediatric patients 12 years of age and older: 1 to 2 mL every four hours or as needed. Do not exceed 12 mL in 24 hours.
Pediatric patients 2 to under 12 years of age: 1/4 to 1 mL every four hours or as needed. Do not exceed 6 mL in 24 hours.
Pediatric patients under 2 years of age: The following dosage guide is based upon body weight. The doses may be repeated every four hours or as needed.

Body Weight | Usual Dose | Do Not Exceed
 |  | In 24 Hours
3.4 kg (7.5 lb.) | 4 drops | 24 drops
5 kg (11 lb.) | 5 drops | 30 drops
7 kg (15 lb.) | 6 drops | 36 drops
10 kg (22 lb.) | 8 drops | 48 drops

Package of Hyoscyamine Sulfate Oral Drops is accompanied with a dropper having markings of 3, 4, 5 DROPS, and 0.25 mL. The approximate equivalent amount of hyoscyamine sulfate drops (mL) and its equivalent amount of hyoscyamine sulfate (mg) for each marking are as follows:

 |  | Approximate Equivalent Amount
Marking on Dropper | Hyoscyamine Sulfate Oral Drops Solution (mL) |  | Hyoscyamine Sulfate (mg)
3 DROPS | 0.08 mL |  | 0.01 mg
4 DROPS | 0.11 mL |  | 0.01375 mg
5 DROPS | 0.14 mL |  | 0.0175 mg
0.25 mL | 0.25 mL |  | 0.03125 mg

HYOSYNE ELIXIR
(Hyoscyamine Sulfate Elixir)
Dosage may be adjusted according to the conditions and severity of symptoms. Measure dosage very carefully.
Adults and pediatric patients 12 years of age and older: 1 to 2 teaspoonfuls every four hours or as needed. Do not exceed 12 teaspoonfuls in 24 hours.
Pediatric patients 2 to under 12 years of age: Please see the following dosage guide is based on body weight. The doses may be repeated every four hours or as needed. Do not exceed 6teaspoonfuls in 24 hours.

Body Weight | Usual Dose
10 kg (22 lb.) | 1/4 teaspoon (1.25 mL)
20 kg (44 lb.) | 1/2 teaspoonful (2.5 mL)
40 kg (88 lb.) | 3/4 teaspoonful (3.75 mL)
50 kg (110 lb.) | 1 teaspoonful (5 mL)

HOW SUPPLIED

Product: 17856-0511

NDC: 17856-0511-1 5 mL in a CUP

NDC: 17856-0511-2 10 mL in a CUP